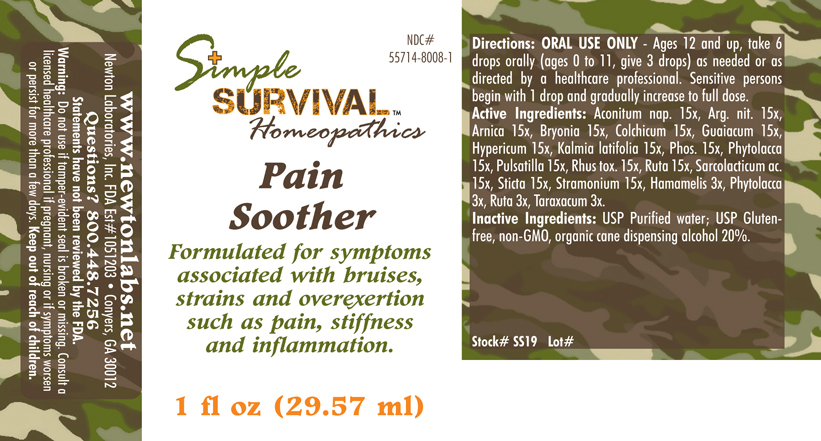 DRUG LABEL: Pain Soother 
NDC: 55714-8008 | Form: LIQUID
Manufacturer: Newton Laboratories, Inc.
Category: homeopathic | Type: HUMAN OTC DRUG LABEL
Date: 20140415

ACTIVE INGREDIENTS: Aconitum Napellus 15 [hp_X]/1 mL; Silver Nitrate 15 [hp_X]/1 mL; Arnica Montana 15 [hp_X]/1 mL; Bryonia Alba Root 15 [hp_X]/1 mL; Colchicum Autumnale Bulb 15 [hp_X]/1 mL; Guaiac 15 [hp_X]/1 mL; Hypericum Perforatum 15 [hp_X]/1 mL; Kalmia Latifolia Leaf 15 [hp_X]/1 mL; Phosphorus 15 [hp_X]/1 mL; Phytolacca Americana Root 15 [hp_X]/1 mL; Pulsatilla Vulgaris 15 [hp_X]/1 mL; Toxicodendron Pubescens Leaf 15 [hp_X]/1 mL; Ruta Graveolens Flowering Top 15 [hp_X]/1 mL; Lactic Acid, L- 15 [hp_X]/1 mL; Lobaria Pulmonaria 15 [hp_X]/1 mL; Datura Stramonium 15 [hp_X]/1 mL; Hamamelis Virginiana Root Bark/stem Bark 3 [hp_X]/1 mL; Taraxacum Officinale 3 [hp_X]/1 mL
INACTIVE INGREDIENTS: Alcohol

Pain Soother

INDICATIONS & USAGE SECTION

Pain Soother Formulated for symptoms associated with bruises, strains and overexertion such as pain, stiffness and inflammation.

DOSAGE & ADMINISTRATION SECTION

Directions: ORAL USE ONLY - Ages 12 and up, take 6 drops orally (ages 0 to 11, give 3 drops) as needed or as directed by a healthcare professional. Sensitive persons begin with 1 drop and gradually increase to full dose.

OTC - ACTIVE INGREDIENT SECTION

Aconitum nap. 15x, Arg. nit. 15x, Arnica 15x, Bryonia 15x, Colchicum 15x, Guaiacum 15x, Hypericum 15x, Kalmia latifolia 15x, Phos. 15x, Phytolacca 15x, Pulsatilla 15x, Rhus tox. 15x, Ruta 15x, Sarcolacticum ac. 15x, Sticta 15x, Stramonium 15x, Hamamelis 3x, Phytolacca 3x, Ruta 3x, Taraxacum 3x.

OTC - PURPOSE SECTION

Formulated for symptoms associated with bruises, strains and overexertion such as pain, stiffness and inflammation.

INACTIVE INGREDIENT SECTION

Inactive Ingredients: USP Purified Water; USP Gluten-free, non-GMO, organic cane dispensing alcohol 20%.

OTC - QUESTIONS SECTION

www.newtonlabs.net Newton Laboratories, Inc. FDA Est # 1051203 - Conyers, GA 30012
Questions? 1.800.448.7256

WARNINGS SECTION

Warning: Do not use if tamper - evident seal is broken or missing. Consult a licensed healthcare professional if pregnant, nursing or if symptoms worsen or persist for more than a few days. Keep out of reach of children.

OTC - PREGNANCY OR BREAST FEEDING SECTION

Consult a licensed healthcare professional if pregnant, nursing or if symptoms worsen or persist for more than a few days.

OTC - KEEP OUT OF REACH OF CHILDREN SECTION

Keep out of reach of children.